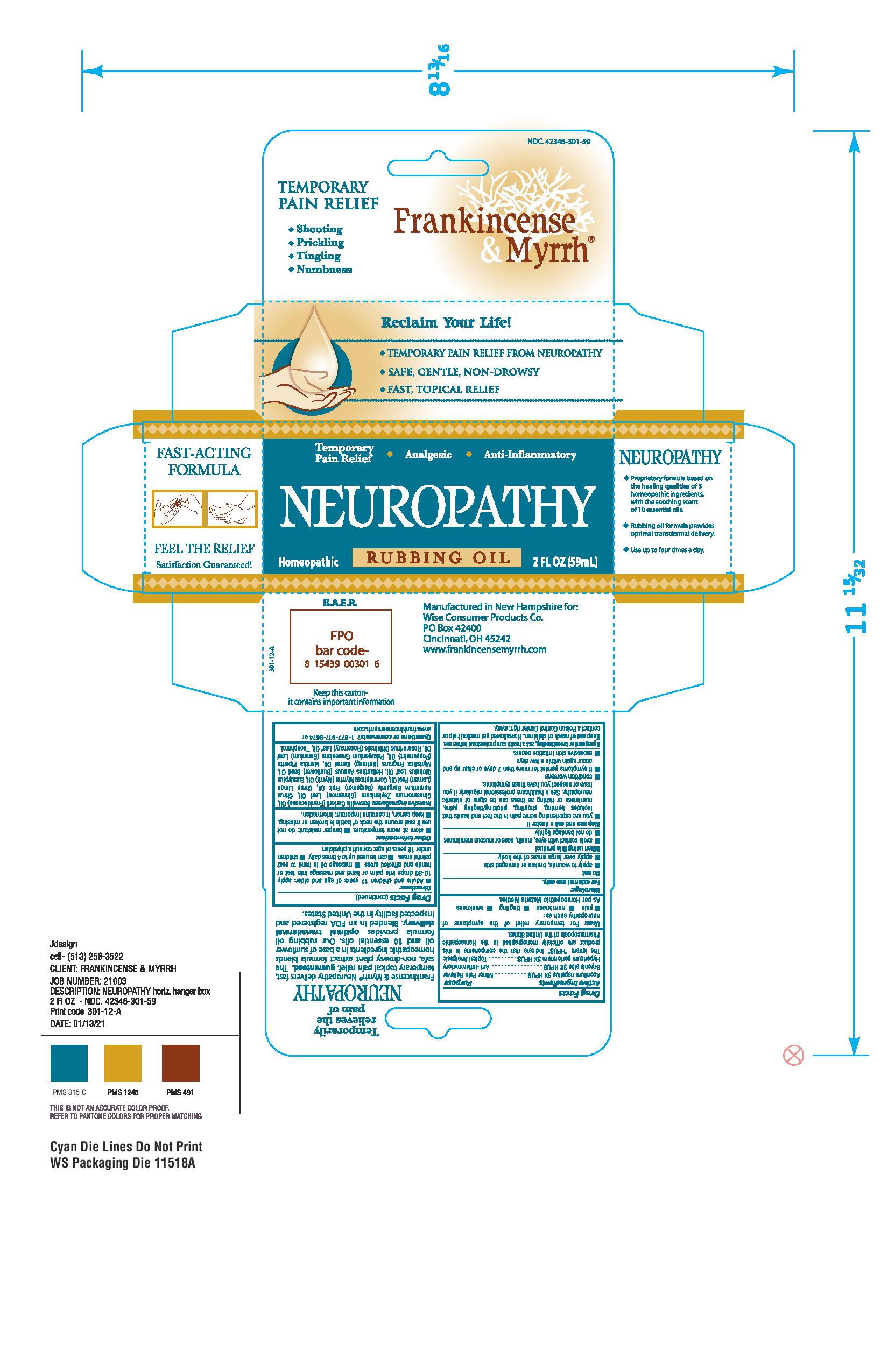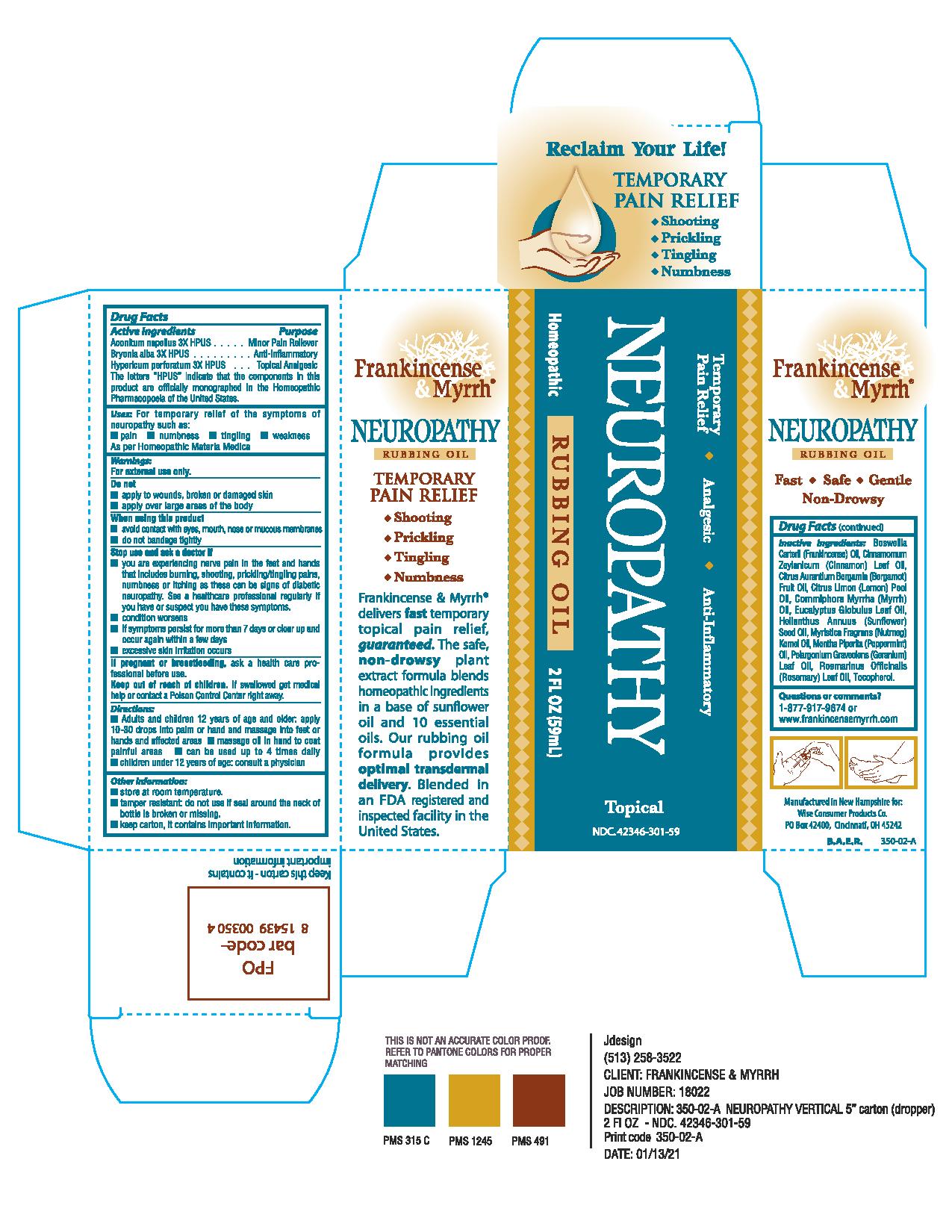 DRUG LABEL: Frankincense and Myrrh Neuropathy
NDC: 42346-301 | Form: OIL
Manufacturer: Wise Consumer Products
Category: homeopathic | Type: HUMAN OTC DRUG LABEL
Date: 20211203

ACTIVE INGREDIENTS: ACONITUM NAPELLUS 3 [hp_X]/59 mL; BRYONIA ALBA ROOT 3 [hp_X]/59 mL; HYPERICUM PERFORATUM 3 [hp_X]/59 mL
INACTIVE INGREDIENTS: BERGAMOT OIL; CINNAMON OIL; EUCALYPTUS OIL; FRANKINCENSE OIL; GERANIUM OIL, ALGERIAN TYPE; LEMON OIL; MYRRH OIL; NUTMEG OIL; PEPPERMINT OIL; ROSEMARY OIL; SUNFLOWER OIL; .ALPHA.-TOCOPHEROL

Drug Facts

Active Ingredients

Aconitum napellus 3X HPUS

Bryonia alba 3X HPUS

Hypericum perforatum 3X HPUS

The letters "HPUS" indicate that the components in this product are officially monographed in the Homeopathic Pharmacopoeia of the United States.

Purpose

Aconitum napellus 3X HPUS...................Minor Pain Reliever
Bryonia alba 3X HPUS............................Anti-inflammatory
Hypericum perforatum 3X HPUS.............Topical Analgesic

Uses:

For temporary relief of the symptoms of neuropathy such as:

- pain
- numbness
- tingling
- weakness

As per Homeopathic Materia Medica

Warnings:

For external use only.

Do not

- apply to wounds, broken or damaged skin
- apply over large areas of the body

When using this product

- avoid contact with eyes, mouth, nose or mucous membranes
- do not bandage tightly

Stop use and ask a doctor if

- you are experiencing nerve pain in the feet and hands that includes burning, shooting, prickling/tingling pains, numbness or itching as these can be signs of diabetic neuropathy. See a healthcare professional regularly if you have or suspect you have these symptoms.
- condition worsens
- if symptoms persist for more than 7 days or clear up and occur again within a few days
- excessive skin irritation occurs

PREGNANCY OR BREAST FEEDING

If pregnant or breastfeeding, ask a health care professional before use.

Keep out of reach of children.

OTHER SAFETY INFORMATION

If swallowed get medical help or contact a Poison Control Center right away.

Directions:

- Adults and children 12 years of age and older: apply 10-30 drops into palm or hand and massage into feet or hands and affected areas
- massage oil in hand to coat painful areas
- can be used up to 4 times daily
- children under 12 years of age: consult a physician

Other Information:

- store at room temperature.
- tamper resistant: do not use if seal around the neck of bottle is broken or missing.
- keep carton, it contains important information.

Inactive Ingredients:

Boswellia Carterii (Frankincense) Oil, Cinnamomum Zeylanicum (Cinnamon) Leaf Oil, Citrus Aurantium Bergamia (Bergamot) Fruit Oil, Citrus Limon (Lemon) Peel Oil, Commiphora Myrrha (Myrrh) Oil, Eucalyptus Globulus Leaf Oil, Helianthus Annuus (Sunflower) Seed Oil, Myristica Fragrans (Nutmeg) Kernel Oil, Mentha Piperita (Peppermint) Oil, Pelargonium Graveolens (Geranium) Leaf Oil, Rosmarinus Officinalis (Rosemary) Leaf Oil, Tocopherol.

Questions or comments?

1-877-917-9674 or www.frankincensemyrrh.com

DESCRIPTION

Manufactured in New Hampshire for:
Wise Consumer Products Co.
PO Box 42400
Cincinnati, OH 45242
www.frankincensemyrrh.com
Keep this carton - it contains important information
Temporarily relieves the pain of NEUROPATHY
Frankincense and MyrrhTM Neuropathy is specifically formulated to deliver temporary and topical relief for Neuropathy. The plant extract formula blends homeopathic ingredients in a base of sunflower oil and 10 essential oils. Blended in an FDA registered and inspected facility in the United States.

Principal Display Panel

NDC. 42346-300-59
TEMPORARY PAIN RELIEF
* Shooting
* Prickling
* Tingling
* Numbness
Frankincense and
MyrrhTM
Reclaim Your Life!
* TEMPORARY PAIN RELIEF FROM NEUROPATHY
* SAFE, GENTLE, NON-DROWSY
* FAST, TOPICAL RELIEF
Temporary Pain Relief - Analgesic - Anti-Inflammatory
NEUROPATHY
Homeopathic RUBBING OIL 2 FL OZ (59 mL)